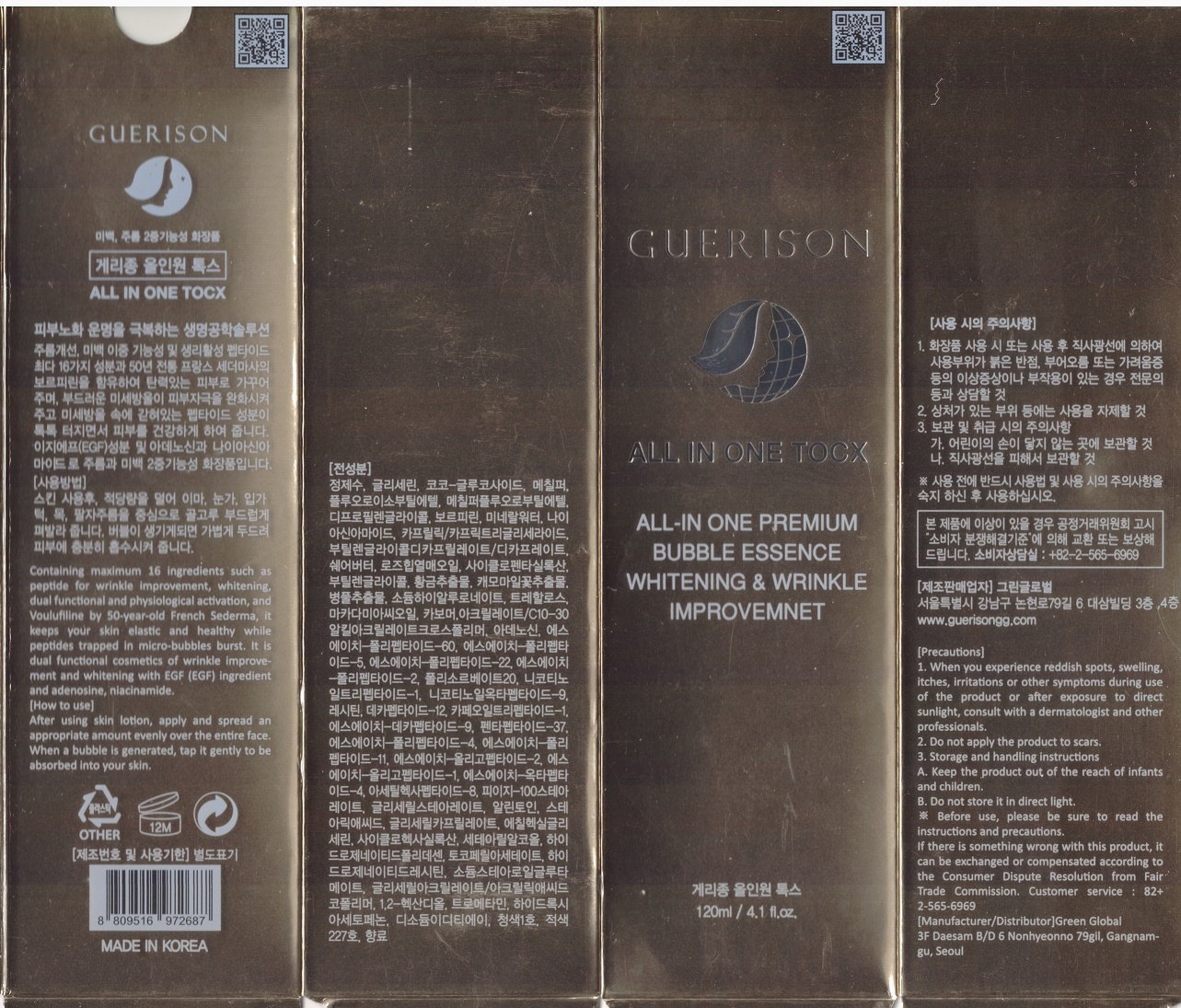 DRUG LABEL: GUERISON ALL IN ONE TOCX
NDC: 73111-0001 | Form: CREAM
Manufacturer: GUERISON GREEN GLOBAL COMPANY LIMITED
Category: otc | Type: HUMAN OTC DRUG LABEL
Date: 20210105

ACTIVE INGREDIENTS: GLYCERIN 5 g/100 mL
INACTIVE INGREDIENTS: WATER; NIACINAMIDE

Drug Facts

ACTIVE INGREDIENT

glycerin

INACTIVE INGREDIENT

Water, niacinamide, butylene glycol, adenosine, etc

PURPOSE

whitening & wrinkle improvement

keep out of reach of the children

INDICATIONS AND USAGE

after using skin lotion, apply and spread an appropriate amount evenly over the entire face

when a bubble is generated, tap it gently to be absorbed into your skin

WARNINGS

■ if following abnormal symptoms occurs after use , stop use and consult with a skin specialist

red specks, swelling, itching

■ don’t use on the part where there is injury, eczema, or dermatitis

Keep out of reach of children

■ if swallowed, get medical help or contact a person control center immediately

DOSAGE AND ADMINISTRATION

for external use only